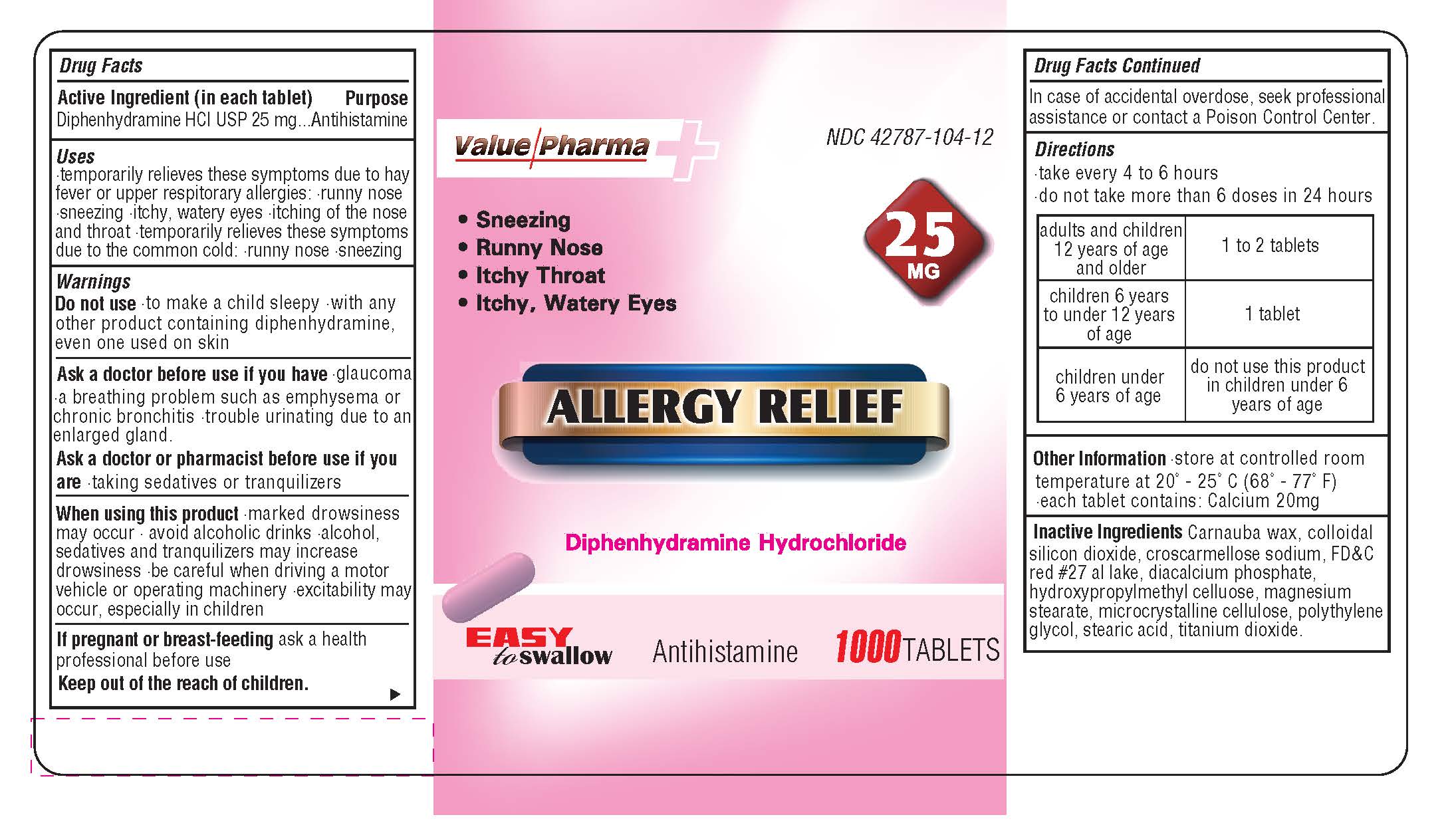 DRUG LABEL: BENALDRYL
NDC: 42787-104 | Form: TABLET
Manufacturer: AJES PHARMACEUTICALS,LLC
Category: otc | Type: HUMAN OTC DRUG LABEL
Date: 20140525

ACTIVE INGREDIENTS: DIPHENHYDRAMINE HYDROCHLORIDE 25 mg/250 mg
INACTIVE INGREDIENTS: CARNAUBA WAX; SILICON DIOXIDE; CROSCARMELLOSE SODIUM; D&C RED NO. 27; CALCIUM PHOSPHATE, DIBASIC, ANHYDROUS; HYPROMELLOSES; MAGNESIUM STEARATE; CELLULOSE, MICROCRYSTALLINE; POLYETHYLENE GLYCOLS; STEARIC ACID; TITANIUM DIOXIDE

Drug Facts

Active Ingredient (in each tablet)

Diphenhydramine HCI USP 25 mg

Purpose

Antihistamine

Keep out of the reach of children

In case of accidental overdose,

seek professional assistance or contact a Poison Control Center

Uses

-temporarily relieves these symptoms due to hay fever or upper

respiratory allergies: runny nose - sneezing - itchy, watery eyes

-itching of the nose and throat - temporarily relieves these

symptoms due to the common cold: runny nose - sneezing

Warnings

Do Not Use - to make a child sleepy - with any other product

containing diphenhydramine, even one used on skin

DOSAGE AND ADMINISTRATION

Directions - take every 4 to 6 hours

-do not take more than 6 doses in 24 hours

adults and children 12 years of age or older - 1 to 2 tablets

children 6 years to under 12 years of age - 1 tablet

children under 6 years of age - do not use this product in children under 6 years of age

INACTIVE INGREDIENT

Enter section text here